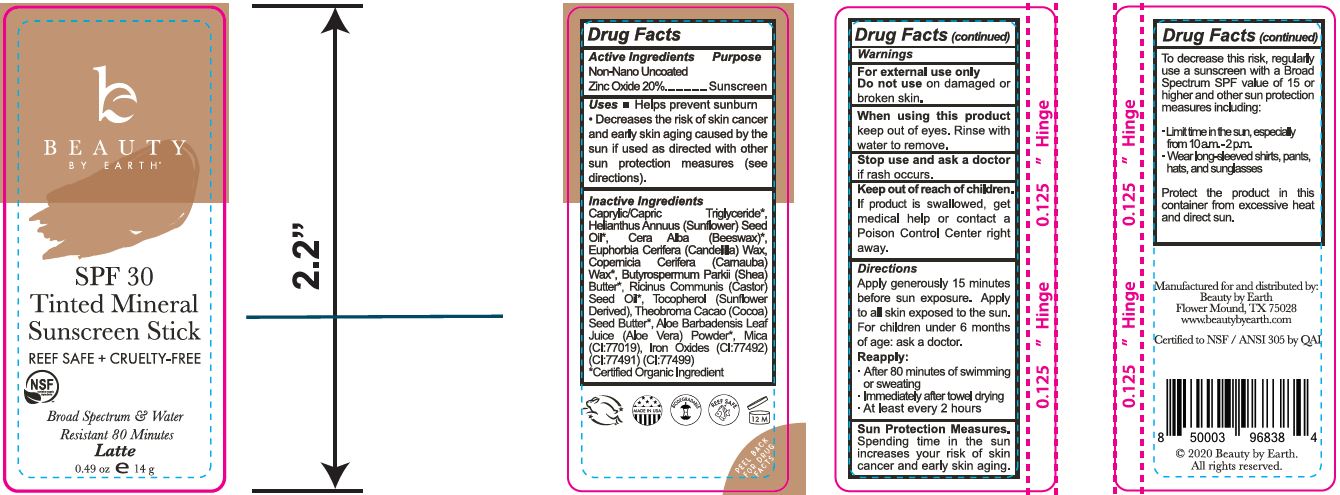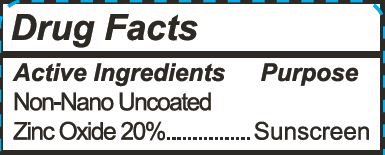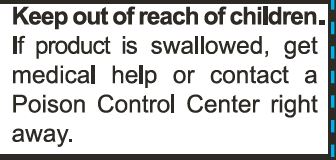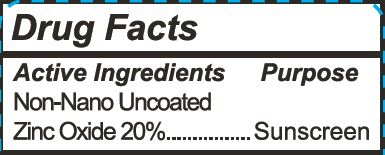 DRUG LABEL: Tinted Mineral Face Sunscreen Stick - Latte
NDC: 62932-222 | Form: STICK
Manufacturer: Private Label Select Ltd CO
Category: otc | Type: HUMAN OTC DRUG LABEL
Date: 20220104

ACTIVE INGREDIENTS: ZINC OXIDE 20 g/100 g
INACTIVE INGREDIENTS: WHITE WAX; CANDELILLA WAX; FERRIC OXYHYDROXIDE; FERROSOFERRIC OXIDE; MEDIUM-CHAIN TRIGLYCERIDES; SUNFLOWER OIL; .DELTA.-TOCOPHEROL; COCOA BUTTER; ALOE VERA LEAF; .GAMMA.-TOCOPHEROL; .ALPHA.-TOCOPHEROL, D-; .BETA.-TOCOPHEROL; CARNAUBA WAX; SHEA BUTTER; FERRIC OXIDE RED; CASTOR OIL; MICA

Beauty By Earth Tinted Mineral Face Sunscreen Stick - Latte